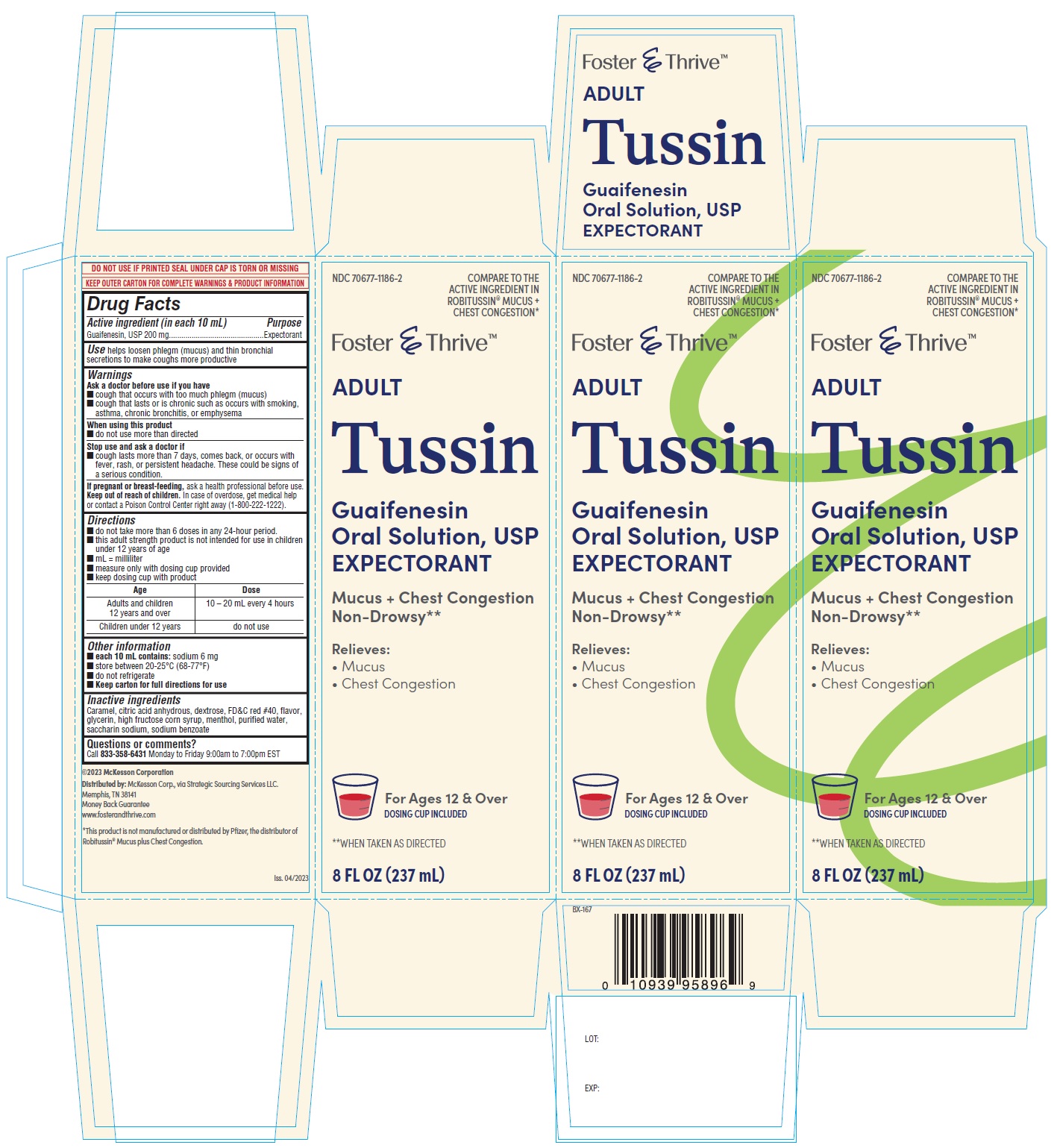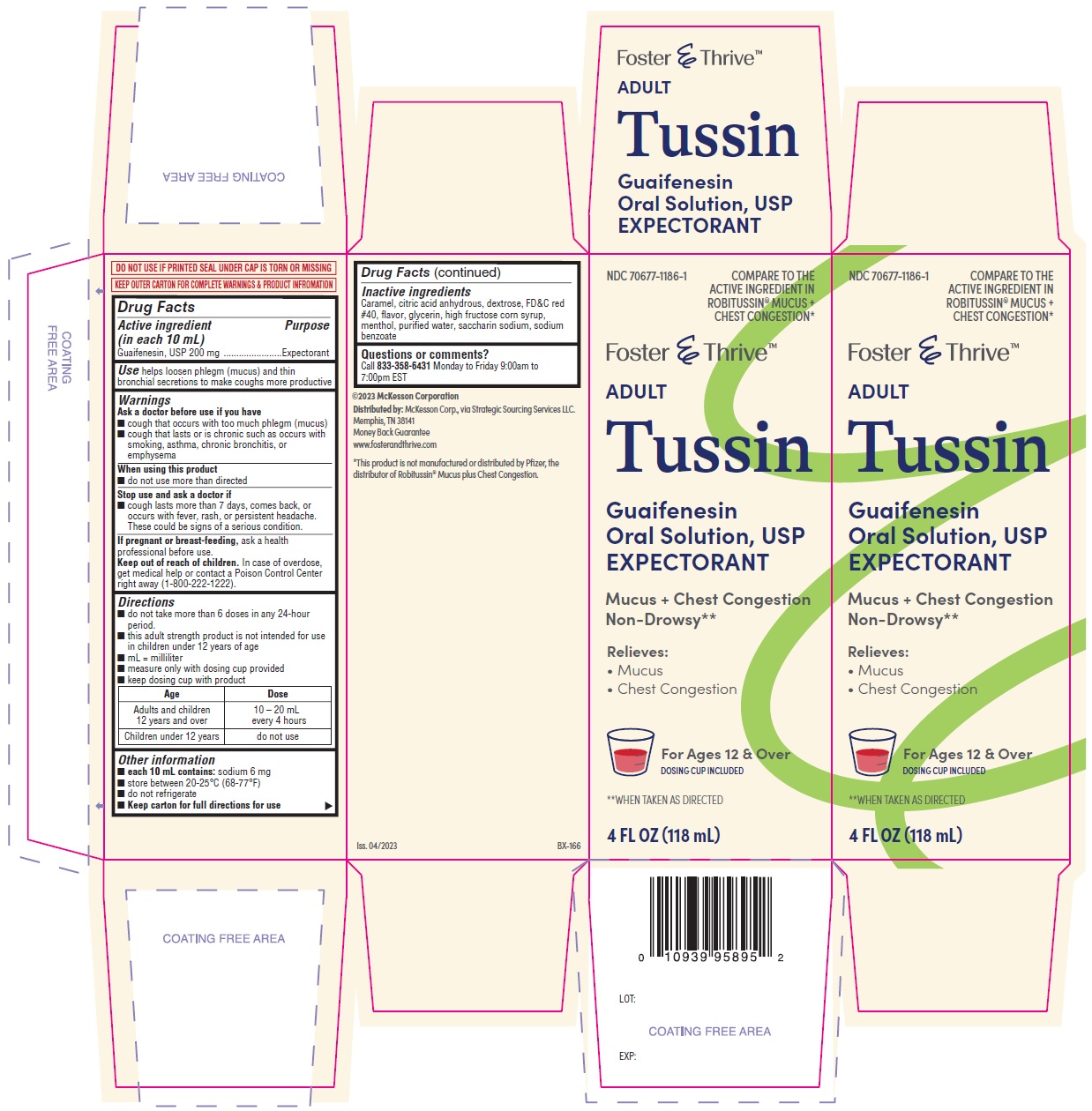 DRUG LABEL: Tussin
NDC: 70677-1186 | Form: SOLUTION
Manufacturer: Strategic Sourcing Services
Category: otc | Type: HUMAN OTC DRUG LABEL
Date: 20250108

ACTIVE INGREDIENTS: GUAIFENESIN 200 mg/10 mL
INACTIVE INGREDIENTS: CARAMEL; ANHYDROUS CITRIC ACID; DEXTROSE; FD&C RED NO. 40; GLYCERIN; HIGH FRUCTOSE CORN SYRUP; MENTHOL; WATER; SACCHARIN SODIUM; SODIUM BENZOATE

Tussin
GuaifenesinOral Solution, USP

ACTIVE INGREDIENT(S)

Guaifenesin, USP 200 mg

PURPOSE

Expectorant

USE(S)

helps loosen phlegm (mucus) and thin bronchial secretions to make coughs more productive

WARNINGS

Ask a doctor before use if you have

■ cough that occurs with too much phlegm (mucus)
■ cough that lasts or is chronic such as occurs with smoking, asthma, chronic bronchitis, or emphysema

WHEN USING THIS PRODUCT

■ do not use more than directed

STOP USE AND ASK DOCTOR IF

■ cough lasts more than 7 days, comes back, or occurs with fever, rash, or persistent headache. These could be signs of a serious condition.

If pregnant or breast-feeding

ask a health professional before use.

KEEP OUT OF REACH OF CHILDREN

In case of overdose, get medical help or contact a Poison Control Center right away (1-800-222-1222).

DIRECTIONS

■ do not take more than 6 doses in any 24-hour period.
■ this adult strength product is not intended for use in children under 12 years of age
■ mL = milliliter
■ measure only with dosing cup provided
■ keep dosing cup with product

Age | Dose
Adults and children 12 years and over | 10 – 20 mL every 4 hours
Children under 12 years | do not use

Other information

■ each 10 mL contains:sodium 6 mg
■ store between 20-25°C (68-77°F)
■ do not refrigerate
■ Keep carton for full directions for use

Inactive ingredients

Caramel, citric acid anhydrous, dextrose, FD&C red #40, flavor, glycerin, high fructose corn syrup, menthol, purified water, saccharin sodium, sodium benzoate

Questions or comments?

Call 833-358-6431Monday to Friday 9:00am to 7:00pm EST

PRINCIPAL DISPLAY PANEL

Guaifenesin oral solution USP-118 mL

Guaifenesin oral solution USP-237 mL